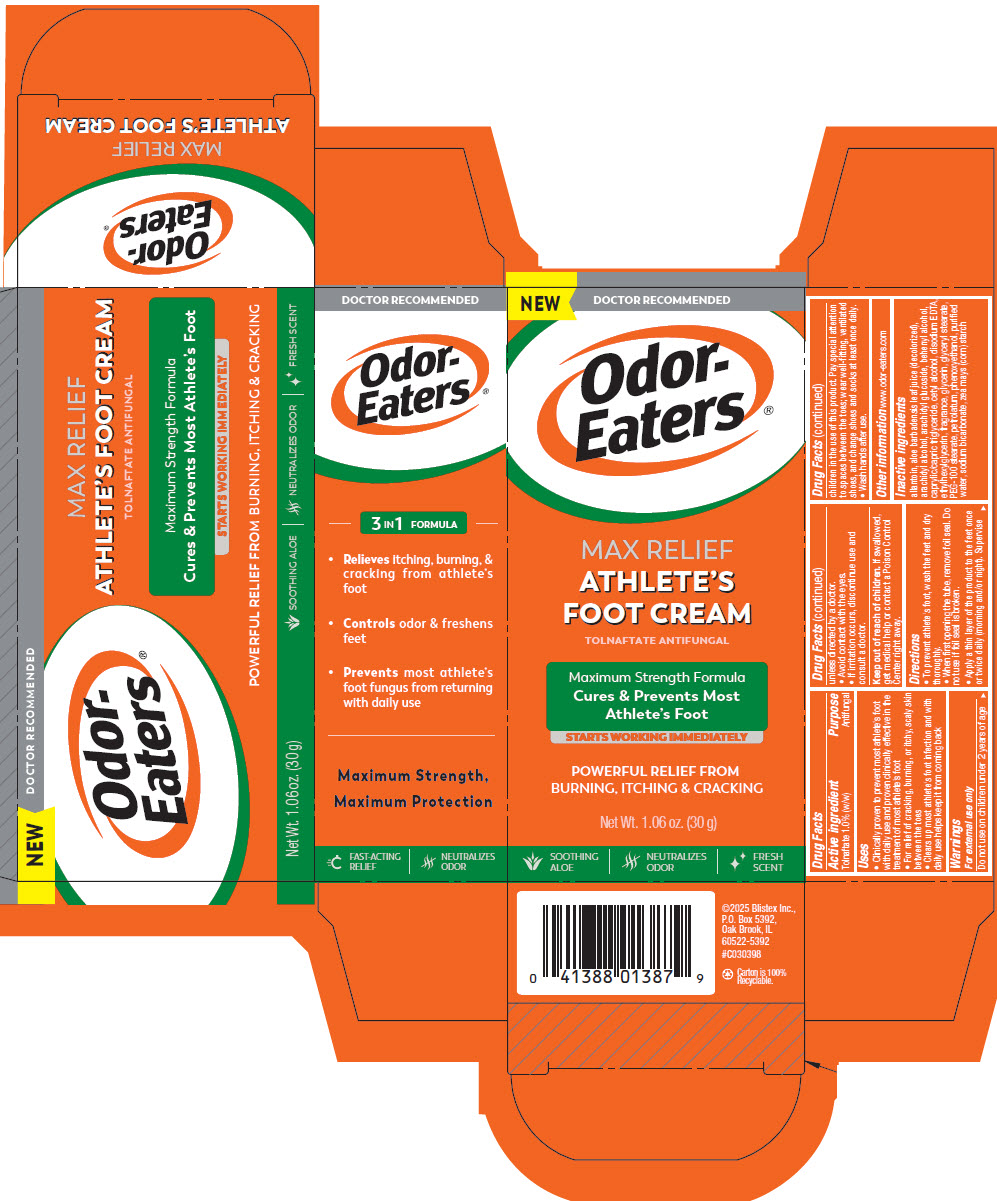 DRUG LABEL: Odor-Eaters Athletes Foot
NDC: 10157-3100 | Form: CREAM
Manufacturer: Blistex Inc.
Category: otc | Type: HUMAN OTC DRUG LABEL
Date: 20251121

ACTIVE INGREDIENTS: TOLNAFTATE 1 g/100 g
INACTIVE INGREDIENTS: WATER; MEDIUM-CHAIN TRIGLYCERIDES; GLYCERYL STEARATE/PEG-100 STEARATE; GLYCERIN; WHITE PETROLATUM; ARACHIDYL ALCOHOL; DOCOSANOL; ARACHIDYL GLUCOSIDE; CETYL ALCOHOL; STARCH, CORN; PHENOXYETHANOL; ETHYLHEXYLGLYCERIN; SODIUM BICARBONATE; EDETATE DISODIUM; ALLANTOIN; ALOE VERA LEAF JUICE

Odor-Eaters® Athlete's Foot Cream

Drug Facts

Active ingredient

Tolnaftate 1.0% (w/w)

Purpose

Antifungal

Uses

- Clinically proven to prevent most athlete's foot with daily use and proven clinically effective in the treatment of most athlete's foot
- For relief of cracking, burning, or itchy, scaly skin between the toes
- Clears up most athlete's foot infection and with daily use helps keep it from coming back

Warnings

For external use only

Do not use on children under 2 years of age unless directed by a doctor.

- Avoid contact with the eyes.
- If irritation occurs, discontinue use and consult a doctor.

Keep out of reach of children. If swallowed, get medical help or contact a Poison Control Center right away.

Directions

- To prevent athlete's foot, wash the feet and dry thoroughly.
- When first opening the tube, remove foil seal. Do not use if foil seal is broken.
- Apply a thin layer of the product to the feet once or twice daily (morning and/or night). Supervise children in the use of this product. Pay special attention to spaces between the toes; wear well-fitting, ventilated shoes, and change shoes and socks at least once daily.
- Wash hands after use.

Other information

www.odor-eaters.com

Inactive ingredients

allantoin, aloe barbadensis leaf juice (decolorized), arachidyl alcohol, arachidyl glucoside, behenyl alcohol, caprylic/capric triglyceride, cetyl alcohol, disodium EDTA, ethylhexylglycerin, fragrance, glycerin, glyceryl stearate, PEG-100 stearate, petrolatum, phenoxyethanol, purified water, sodium bicarbonate, zea mays (corn) starch

PRINCIPAL DISPLAY PANEL - 30 g Tube Carton

NEW

DOCTOR RECOMMENDED

Odor-
Eaters®

MAX RELIEF
ATHLETE'S
FOOT CREAM

TOLNAFTATE ANTIFUNGAL

Maximum Strength Formula

Cures & Prevents Most
Athlete's Foot

STARTS WORKING IMMEDIATELY

POWERFUL RELIEF FROM
BURNING, ITCHING & CRACKING

Net Wt. 1.06 oz. (30 g)

SOOTHING
ALOE

NEUTRALIZES
ODOR

FRESH
SCENT